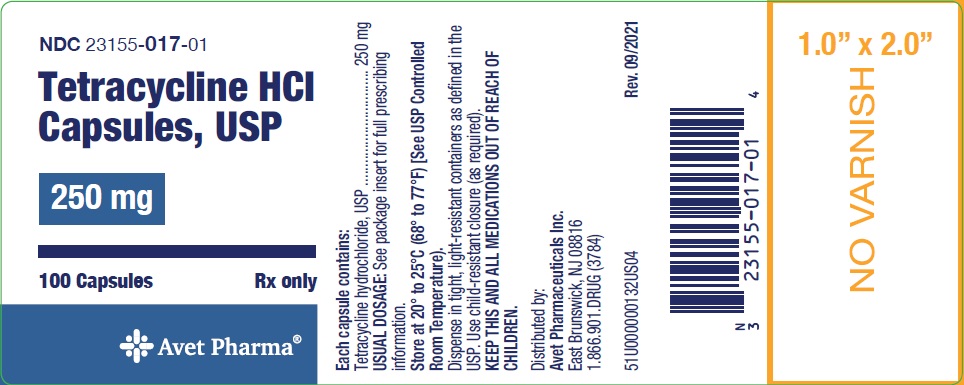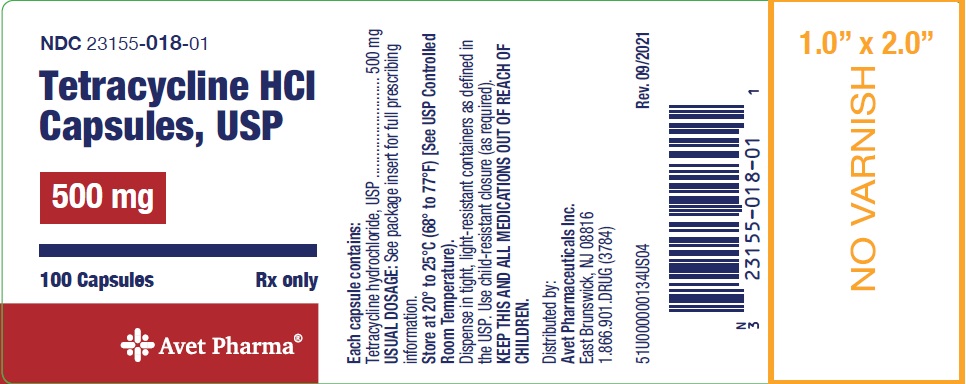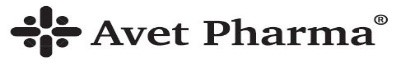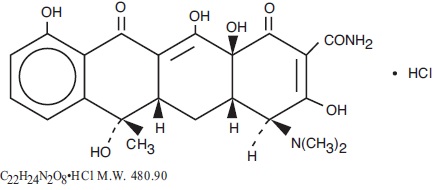 DRUG LABEL: tetracycline hydrochloride
NDC: 23155-017 | Form: CAPSULE
Manufacturer: Heritage Pharmaceuticals Inc. d/b/a Avet Pharmaceuticals Inc.
Category: prescription | Type: HUMAN PRESCRIPTION DRUG LABEL
Date: 20250318

ACTIVE INGREDIENTS: TETRACYCLINE HYDROCHLORIDE 250 mg/1 1
INACTIVE INGREDIENTS: LACTOSE MONOHYDRATE; LIGHT MINERAL OIL; MAGNESIUM STEARATE; D&C YELLOW NO. 10; FD&C BLUE NO. 1; FD&C YELLOW NO. 6; GELATIN, UNSPECIFIED; TITANIUM DIOXIDE; FD&C BLUE NO. 2; FD&C RED NO. 40; SHELLAC; PROPYLENE GLYCOL; BUTYL ALCOHOL; FERROSOFERRIC OXIDE

For Oral Use
Rx only

To reduce the development of drug-resistant bacteria and maintain the effectiveness of tetracycline hydrochloride and other antibacterial drugs, tetracycline hydrochloride should be used only to treat or prevent infections that are proven or strongly suspected to be caused by bacteria.

DESCRIPTION

Tetracycline is a yellow, odorless, crystalline powder. Tetracycline is stable in air but exposure to strong sunlight causes it to darken. Its potency is affected in solutions of pH below 2 and is rapidly destroyed by alkali hydroxide solutions. Tetracycline is very slightly soluble in water, freely soluble in dilute acid and in alkali hydroxide solutions, sparingly soluble in alcohol, and practically insoluble in chloroform and in ether. The chemical name for tetracycline hydrochloride is 4-(Dimethylamino)-1,4,4a,5,5a,6,11,12a-octahydro-3,6,10,12,-12a-pentahydroxy-6-methyl-1,11-dioxo-2-naphthacenecarboxamide monohydrochloride. Its structural formula is as follows:

Each capsule, for oral administration, contains 250 mg or 500 mg tetracycline hydrochloride.

Inactive Ingredients: Lactose, light mineral oil, and magnesium stearate.

The 250 mg and 500 mg capsule shells contain D&C yellow no. 10, FD&C blue no. 1, FD&C yellow no. 6, gelatin, and titanium dioxide.

The imprinting ink for the 250 mg and 500 mg capsules contains D&C yellow #10, FD&C blue no. 1, FD&C blue no. 2, FD&C red no. 40, iron oxide black, pharmaceutical shellac glaze, propylene glycol and n-butyl alcohol.

CLINICAL PHARMACOLOGY

Tetracyclines are readily absorbed and are bound to plasma protein in varying degrees. They are concentrated by the liver in the bile and excreted in the urine and feces at high concentrations in a biologically active form.

Microbiology

Tetracyclines are primarily bacteriostatic and exert their antimicrobial effect by the inhibition of protein synthesis by binding to the 30S ribosomal subunit. Tetracycline is active against a broad range of gram-negative and gram-positive organisms. The drugs in the tetracycline class have closely similar antimicrobial spectra, and cross-resistance among them is common.

Tetracycline has been shown to be active against most isolates of the following bacteria, both in vitro and in clinical infections as described in the INDICATIONS AND USAGE section of the package insert.

Gram-negative Bacteria

Acinetobacter species

Bartonella bacilliformis

Brucella species

Campylobacter fetus

Enterobacter aerogenes

Escherichia coli

Francisella tularensis

Haemophilus ducreyi

Haemophilus influenzae

Klebsiella species

Klebsiella granulomatis

Neisseria gonorrhoeae

Shigella species

Vibrio cholerae

Yersinia pestis

Gram-positive Bacteria

Bacillus anthracis

Streptococcus pyogenes

Streptococcus pneumoniae

Staphylococcus aureus

Listeria monocytogenes

Anaerobes

Bacteroides species

Clostridium species

Fusobacterium fusiforme

Propionibacterium acnes

Other Bacteria

Actinomyces species

Borrelia recurrentis

Chlamydophila psittaci

Chlamydia trachomatis

Rickettsiae

Treponema pallidum

Treponema pallidum subspecies pertenue

Parasites

Entamoeba species

Balantidium coli

Susceptibility Testing

For specific information regarding susceptibility test interpretive criteria and associated test methods and quality control standards recognized by FDA for this drug, please see: https://www.fda.gov/STIC.

INDICATIONS AND USAGE

To reduce the development of drug-resistant bacteria and maintain the effectiveness of tetracycline hydrochloride and other antibacterial drugs, tetracycline hydrochloride should be used only to treat infections that are proven or strongly suspected to be caused by susceptible bacteria. When culture and susceptibility information are available, they should be considered in selecting or modifying antibacterial therapy. In the absence of such data, local epidemiology and susceptibility patterns may contribute to the empiric selection of therapy.

Tetracycline is indicated in the treatment of infections caused by susceptible strains of the designated organisms in the conditions listed below:

- Upper respiratory tract infections caused by Streptococcus pyogenes, Streptococcus pneumoniae and Hemophilus influenzae. Note: Tetracycline should not be used for streptococcal disease unless the organism has been demonstrated to be susceptible.
- Lower respiratory tract infections caused by Streptococcus pyogenes, Streptococcus pneumoniae, Mycoplasma pneumoniae (Eaton agent, and Klebsiella sp.)
- Skin and soft tissue infections caused by Streptococcus pyogenes, Staphylococcus aureaus . (Tetracyclines are not the drugs of choice in the treatment of any type of staphylococcalinfections.)
- Infections caused by rickettsia including Rocky Mountain spotted fever, typhus group infections, Q fever, rickettsialpox.
- Psittacosis caused by Chlamydophila psittaci.
- Infections caused by Chlamydia trachomatis such as uncomplicated urethral, endocervical or rectal infections, inclusion conjunctivitis, trachoma, and lymphogranuloma venereum.
- Granuloma inquinale caused by Klebsiella granulomatis.
- Relapsing fever caused by Borrelia sp.
- Bartonellosis caused by Bartonella bacilliformis .
- Chancroid caused by Hemophilus ducreyi .
- Tularemia caused by Francisella tularensis.
- Plaque caused by Yersinia pestis .
- Cholera caused by Vibrio cholerae.
- Brucellosis caused by Brucella species (tetracycline may be used in conjunction with an aminoglycoside).
- Infections due to Campylobacter fetus .
- As adjunctive therapy in intestinal amebiasis caused by Entamoeba histolytica .
- Urinary tract infections caused by susceptible strains of Escherichia coli, Klebsiella, etc.
- Other infections caused by susceptible gram-negative organisms such as E. coli, Enterobacter aerogenes, Shigellasp., Acinetobacter sp., Klebsiellasp., and Bacteroides sp.
- In severe acne, adjunctive therapy with tetracycline may be useful.

When penicillin is contraindicated, tetracyclines are alternative drugs in the treatment of the following infections:

- Syphilis and yaws caused by Treponema pallidum and pertenue, respectively,
- Vincent's infection caused by Fusobacterium fusiforme,
- Infections caused by Neisseria gonorrhoeae,
- Anthrax caused by Bacillusanthracis,
- Infections due to Listeria monocytogenes,
- Actinomycosis caused by Actinomyces species,
- Infections due to Clostridium species.

CONTRAINDICATIONS

This drug is contraindicated in persons who have shown hypersensitivity to any of the tetracyclines.

WARNINGS

Tooth Development

The use of drugs of the tetracycline-class during tooth development (last half of pregnancy, infancy and childhood to the age of 8 years) may cause permanent discoloration of the teeth (yellow-gray-brown). This adverse reaction is more common during long-term use of the drugs but it has been observed following repeated short-term courses. Enamel hypoplasia has also been reported. Tetracycline drugs should not be used in this age group, except for anthrax, unless other drugs are not likely to be effective or are contraindicated.

Clostridium difficile Associated Diarrhea

Clostridium difficile associated diarrhea (CDAD) has been reported with use of nearly all antibacterial agents, including tetracyclines, and may range in severity from mild diarrhea to fatal colitis. Treatment with antibacterial agents alters the normal flora of the colon leading to overgrowth of C. difficile.

C. difficile produces toxins A and B which contribute to the development of CDAD. Hypertoxin producing strains of C. difficile cause increased morbidity and mortality, as these infections can be refractory to antimicrobial therapy and may require colectomy. CDAD must be considered in all patients who present with diarrhea following antibacterial drugs. Careful medical history is necessary since CDAD has been reported to occur over two months after the administration of antibacterial agents.

If CDAD is suspected or confirmed, ongoing use of antibacterial drugs not directed against C. difficile need to be discontinued. Appropriate fluid and electrolyte management, protein supplementation, antibacterial treatment of C. difficile, and institute surgical evaluation clinically indicated.

Photosensitivity

Photosensitivity manifested by an exaggerated sunburn reaction has been observed in some individuals taking tetracyclines. Advise patients apt to be exposed to direct sunlight or ultraviolet lights that this reaction can occur with tetracycline drugs. Discontinue treatment at the first evidence of skin erythema.

Fixed Drug Eruption

Fixed drug eruptions have occurred with tetracycline and have been associated with worsening severity upon subsequent administrations, including generalized bullous fixed drug eruption (see ADVERSE REACTIONS). If severe skin reactions occur, discontinue tetracycline hydrochloride capsules immediately and institute appropriate therapy.

Intracranial Hypertension

Intracranial hypertension (IH, pseudotumor cerebri) has been associated with the use of tetracyclines including Achromycin V. Clinical manifestations of IH include headache, blurred vision, diplopia, and vision loss; papilledema can be found on fundoscopy. Women of childbearing age who are overweight or have a history of IH are at greater risk for developing tetracycline associated IH. Concomitant use of isotretinoin and tetracycline should be avoided because isotretinoin, a systemic retinoid, is also known to cause pseudotumor cerebri.

Although IH typically resolves after discontinuation of treatment, the possibility for permanent visual loss exists. If visual disturbance occurs during treatment, prompt ophthalmologic evaluation is warranted. Since intracranial pressure can remain elevated for weeks after drug cessation patients should be monitored until they stabilize.

Skeletal Development

All tetracyclines form a stable calcium complex in any bone forming tissue. A decrease in fibula growth rate has been observed in premature infants given oral tetracycline in doses of 25 mg/kg every six hours. This reaction was shown to be reversible when the drug was discontinued.

Results of animal studies indicate that tetracyclines cross the placenta, are found in fetal tissues and can have toxic effects on the developing fetus (often related to retardation of skeletal development). Evidence of embryotoxicity has also been noted in animals treated early in pregnancy. If this drug is used during pregnancy or if the patient becomes pregnant while taking this drug, apprise the patient of the potential hazard to the fetus. Tetracycline drugs should not be used during pregnancy unless absolutely necessary.

Antianabolic Action

The antianabolic action of the tetracyclines may cause an increase in BUN. While this is not a problem in those with normal renal function, in patients with significantly impaired renal function, higher serum levels of tetracycline may lead to azotemia, hyperphosphatemia and acidosis.

Laboratory Monitoring for Long-Term Therapy

In long-term therapy, perform periodic laboratory evaluation of organ systems, including hematopoietic, renal and hepatic studies. If renal impairment exists, even usual oral or parenteral doses may lead to excessive systemic accumulation of the drug and possible liver toxicity. Under such conditions, lower than usual total doses are indicated, and, if therapy is prolonged, serum level determinations of the drug may be advisable.

PRECAUTIONS

General

As with other antibacterials, use of this drug may result in overgrowth of nonsusceptible organisms, including fungi. If superinfection occurs, discontinue antibacterial and institute appropriate therapy.

Treat all infections due to Group A beta-hemolytic streptococci for at least ten days.

Perform incision and drainage or other surgical procedures in conjunction with antibacterial therapy, when indicated.

Prescribing tetracycline in the absence of proven or strongly suspected bacterial infection or a prophylactic indication is unlikely to provide benefit to the patient and increases the risk of the development of drug-resistant bacteria.

Information for Patients

Counsel patients that antibacterial drugs including tetracycline should only be used to treat bacterial infections. They do not treat viral infections (e.g., the common cold). When tetracycline is prescribed to treat a bacterial infection, tell patients that although it is common to feel better early in the course of therapy, the medication should be taken exactly as directed. Skipping doses or not completing the full course of therapy may (1) decrease the effectiveness of the immediate treatment and (2) increase the likelihood that bacteria will develop resistance and will not be treatable by tetracycline or other antibacterial drugs in the future.

Laboratory Tests

In sexually transmitted infections, when coexistent syphilis is suspected, perform dark field examinations before treatment is started and the blood serology repeated monthly for at least four months.

Drug Interactions

Since bacteriostatic drugs may interfere with the bactericidal action of penicillin, it is advisable to avoid giving tetracycline in conjunction with penicillin or other bactericidal antibacterials.

Because the tetracyclines have been shown to depress plasma prothrombin activity, patients who are on anticoagulant therapy may require downward adjustment of their anticoagulant dosage.

Absorption of tetracyclines is impaired by antacids containing aluminum, calcium or magnesium and preparations containing iron, zinc, or sodium bicarbonate.

Concurrent use of tetracycline may render oral contraceptives less effective.

Carcinogenesis, Mutagenesis, Impairment of Fertility

Long-term animal studies are currently being conducted to determine whether tetracycline hydrochloride has carcinogenic potential. Some related antibacterials (oxytetracycline, minocycline) have shown evidence of oncogenic activity in rats.

In two in vitro mammalian cell assay systems (L 51784y mouse lymphoma and Chinese hamster lung cells), there was evidence of mutagenicity with tetracycline hydrochloride.

Tetracycline hydrochloride had no effect on fertility when administered in the diet to male and female rats at a daily intake of approximately 400 mg/kg/day, roughly 8 times the highest recommended human dose based on body surface area.

Pregnancy

Teratogenic Effects

Pregnancy Category D

(see WARNINGS)

Nonteratogenic Effects

(see WARNINGS)

Pregnant women with renal disease may be more prone to develop tetracycline-associated liver failure.

Labor and Delivery

The effect of tetracyclines on labor and delivery is unknown.

Nursing Mothers

Because of potential for serious adverse reaction in nursing infants from tetracyclines, a decision should be made whether to discontinue the drug, taking into account the importance of the drug to the mother (see WARNINGS).

Pediatric Use

See WARNINGS and DOSAGE AND ADMINISTRATION.

ADVERSE REACTIONS

Gastrointestinal: anorexia, nausea, epigastric distress, vomiting, diarrhea, glossitis, black hairy tongue, dysphagia, enterocolitis, and inflammatory lesions (with Candida overgrowth) in the anogenital region.

Esophagitis and esophageal ulceration have been reported in patients receiving particularly the capsule and also the tablet forms of tetracyclines.

Most of the patients were reported to have taken medication immediately before going to bed (see DOSAGE AND ADMINISTRATION).

Teeth: permanent discoloration of teeth may be caused during tooth development. Enamel hypoplasia has been reported (see WARNINGS).

Skin: fixed drug eruption, maculopapular and erythematous rashes. Exfoliative dermatitis has been reported. Onycholysis and discoloration of the nails have been reported. Photosensitivity is discussed in WARNINGS.

Renal Toxicity: an increase in BUN has been reported and is dose related.

Liver: hepatotoxicity and liver failure have been observed in patients receiving tetracycline and in tetracycline-treated patients with renal impairment.

Hypersensitivity Reactions: urticaria, angioneurotic edema, anaphylaxis, anaphylactoid purpura, pericarditis, exacerbation of systemic lupus erythematosus, and serum sickness-like reactions, as fever, rash, and arthralgia.

Blood: hemolytic anemia, thrombocytopenia, thrombocytopenic purpura, neutropenia and eosinophilia have been reported.

When given over prolonged periods, tetracyclines have been reported to produce brown-black microscopic discoloration of thyroid glands. No abnormalities of thyroid function studies are known to occur.

OVERDOSAGE

In case of overdosage, discontinue medication, treat symptomatically and institute supportive measures. Tetracycline is not dialyzable.

DOSAGE AND ADMINISTRATION

Adults: Usual daily dose, 1 gram as 500 mg twice a day or 250 mg four times a day. Higher doses such as 500 mg four times a day may be required for severe infections or for those infections which do not respond to the smaller doses.

For pediatric patients above eight years of age: Usual daily dose, 10 mg/lb to 20 mg/lb (25mg/kg to 50 mg/kg) body weight divided in four equal doses.

Administration of adequate amounts of fluid with the capsule formulation of tetracycline is recommended to wash down the drug and reduce the risk of esophageal irritation and ulceration (see ADVERSE REACTIONS).

Absorption of tetracycline is impaired by antacids containing aluminum, calcium or magnesium and preparations containing iron, zinc or sodium bicarbonate. Food and some dairy products also interfere with absorption.

When used in streptococcal infections, therapy should be continued for 10 days.

For treatment of brucellosis, 500 mg tetracycline four times a day for three weeks accompanied by streptomycin, 1 gram intramuscularly twice daily the first week and once daily the second week.

For the treatment of syphilis in patients allergic to penicillin, the following dosage of tetracycline is recommended: early syphilis (less than one year's duration), 500 mg four times a day for 15 days. Syphilis of more than one year's duration (except neurosyphilis), 500 mg four times a day for 30 days.

For treatment of gonorrhea, the recommended dose is 500 mg by mouth four times a day for seven days.

Uncomplicated urethral, endocervical or rectal infections in adults caused by Chlamydiatrachomatis: 500 mg, by mouth, four times a day for at least seven days.

In cases of moderate to severe acne which, in the judgement of the clinician, require long-term treatment, the recommended initial dosage is 1 gram daily in divided doses. When improvement is noted, reduce dosage gradually to maintenance levels ranging from 125 mg to 500 mg daily. In some patients it may be possible to maintain adequate remission of lesions with alternate day or intermittent therapy. Tetracycline therapy of acne should augment the other standard measures known to be of value. Duration of long-term treatment which can safely be recommended has not been established (see WARNINGS and Carcinogenesis, Mutagenesis, Impairment of Fertility).

Use in Specific Population

In patients with renal impairment (see WARNINGS): decrease total dosage by reduction of recommended individual doses and/or by extending time intervals between doses.

HOW SUPPLIED

Tetracycline Hydrochloride Capsules, USP are available as:

250 mg: Light Blue Opaque Cap/Yellow Opaque Body, Cap and Body Imprinted HP 17 in Black Ink.

Available in bottles of:

100 NDC 23155-017-01

500 mg: Light Blue Opaque Cap/Yellow Opaque Body, Cap and Body Imprinted HP 18 in Black Ink.

Available in bottles of:

100 NDC 23155-018-01

Dispense in a tight, light-resistant container as defined in the USP. Use child-resistant closure (as required).

Store at 20° to 25°C (68° to 77°F) [See USP Controlled Room Temperature].

Call your doctor for medical advice about side effects. You may report side effects to FDA at 1-800-FDA-1088.

ANIMAL PHARMACOLOGY AND ANIMAL TOXICOLOGY

Hyperpigmentation of the thyroid has been produced by members of the tetracycline class in the following species: in rats by oxytetracycline, doxycycline, minocycline, tetracycline PO4 and methacycline; in minipigs by doxycycline, minocycline, tetracycline PO4 and methacycline; in dogs by doxycycline and minocycline; in monkeys by minocycline.

Minocycline, tetracycline PO4, methacycline, doxycycline, tetracycline base, oxytetracycline HCl and tetracycline HCl were goitrogenic in rats fed a low iodine diet. This goitrogenic effect was accomplished by high radioactive iodine uptake. Administration of minocycline also produced a large goiter with high radioiodine uptake in rats fed a relatively high iodine diet.

Treatment of various animal species with this class of drugs has also resulted in the induction of thyroid hyperplasia in the following: in rats and dogs (minocycline), in chickens (chlortetracycline) and in rats and mice (oxytetracycline). Adrenal gland hyperplasia has been observed in goats and rats treated with oxytetracycline.

Rx only

Distributed by:

Avet Pharmaceuticals Inc.

East Brunswick, NJ 08816

1-866-901-DRUG (3784)

Revised: 03/2025

PACKAGE LABEL.PRINCIPAL DISPLAY PANEL - 250 mg

NDC 23155-017-01

Tetracycline HCl Capsules, USP

250 mg

100 Capsules

Rx only

PACKAGE LABEL.PRINCIPAL DISPLAY PANEL - 500 mg

NDC 23155-018-01

Tetracycline HCl Capsules, USP

500 mg

100 Capsules

Rx only